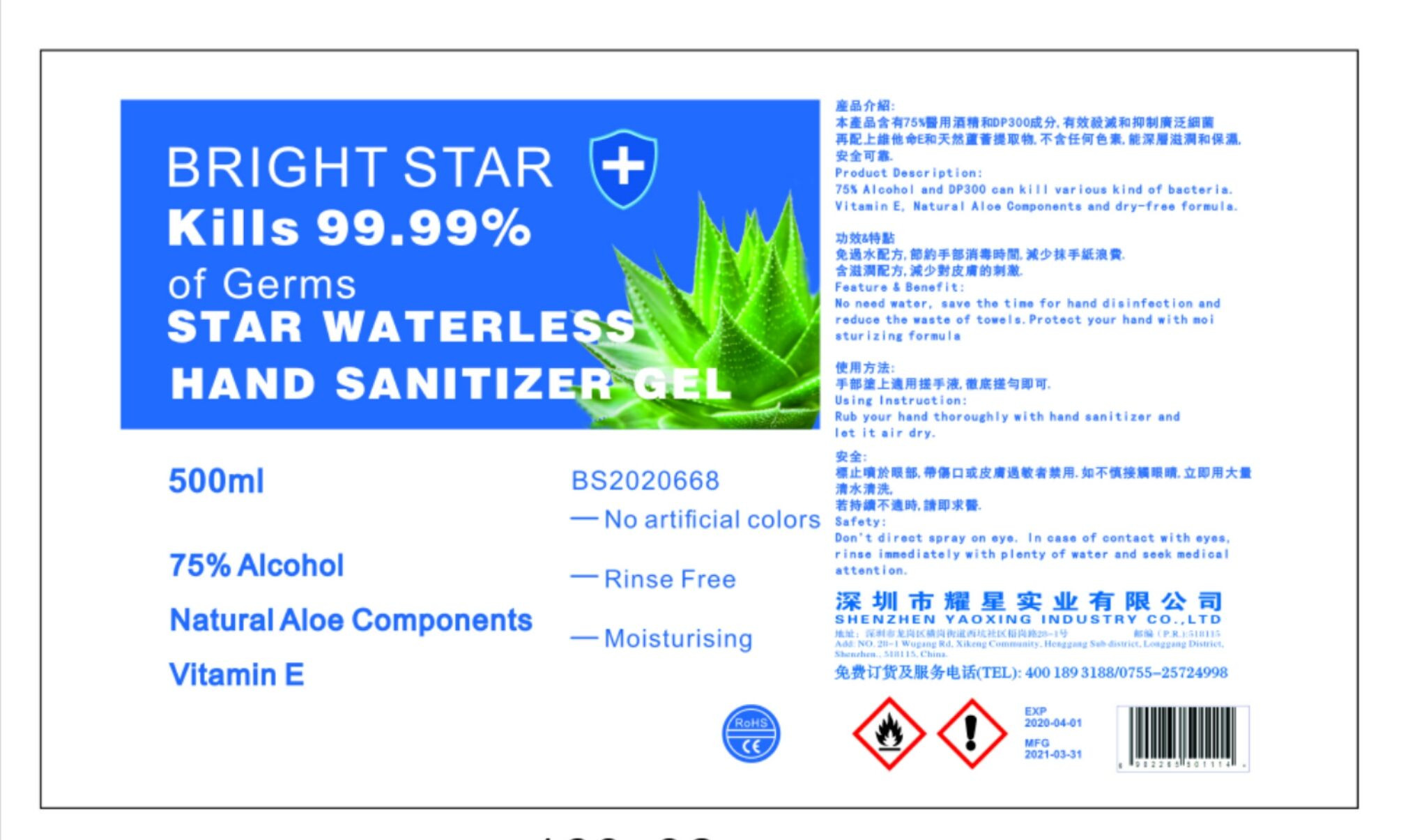 DRUG LABEL: STAR WATERLESS HAND SANITIZERGEL
NDC: 52688-001 | Form: GEL
Manufacturer: Shenzhen City Yaoxing Industry Corp., Ltd
Category: otc | Type: HUMAN OTC DRUG LABEL
Date: 20200514

ACTIVE INGREDIENTS: ALCOHOL 375 mL/500 mL
INACTIVE INGREDIENTS: ALOE; PROPYLENE GLYCOL; TRICLOSAN; TROLAMINE; WATER

DOSAGE AND ADMINISTRATION

store in a cool place

INACTIVE INGREDIENT

TRIETHANOLAMINE

TRICLOSAN

PROPHYLENE GLYCOL

WATER

Aloe extract

INDICATIONS AND USAGE

Rub your hand thoroughly with hand sanitizer and let it air dry.

ACTIVE INGREDIENT

Ethyl alcohol

keep out of reach of children

PURPOSE

Disinfection
Sterilization
No Rinseing

WARNINGS

Don't direct spray on eye. In case of contact with eyes,rinse imnediately with plenty of water and seek medicaI attention.